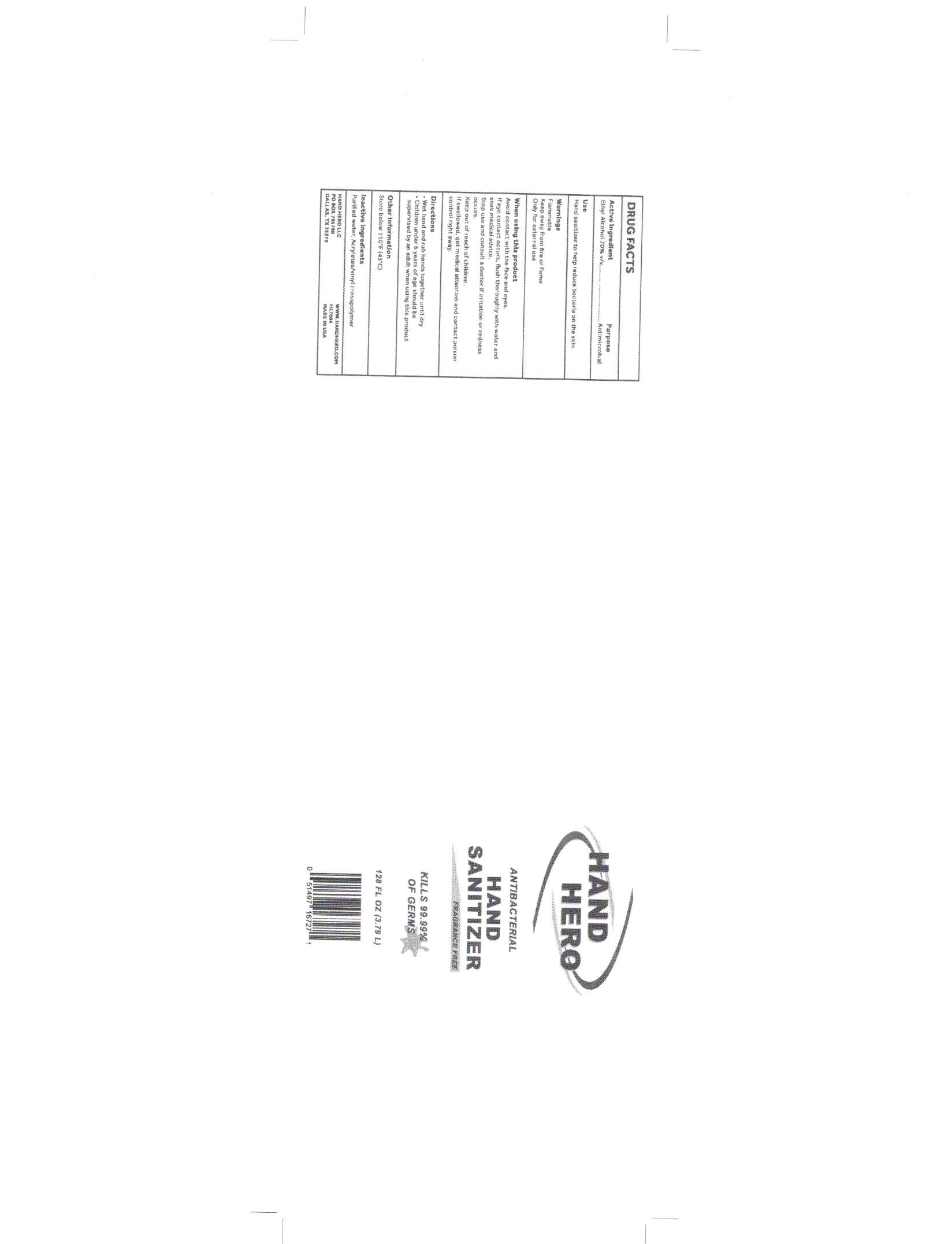 DRUG LABEL: Hand Hero Hand Sanitizer
NDC: 79458-000 | Form: GEL
Manufacturer: Natural Technology, LLC
Category: otc | Type: HUMAN OTC DRUG LABEL
Date: 20220118

ACTIVE INGREDIENTS: ALCOHOL 72 mL/100 mL
INACTIVE INGREDIENTS: WATER 23 mL/100 mL; RAPIDGEL EZ1 5 mL/100 mL

Ethyl Alcohol 70%. Purpose: Antimicrobial

3.79 L Label NDC: 79458-000-02

Purpose: Antimicrobial

3.79 L Label NDC: 79458-000-02

Hand Sanitizer to help reduce bacteria on the skin

3.79 L Label NDC: 79458-000-02

Flammable Keep away from fire or flame Only for external use

3.79 L Label NDC: 79458-000-02

Avoid contact with the face and eyes. If eye contact occurs, flush thoroughly with water and seek medical advice. Stop use and consult a doctor if irritation or redness occurs.

3.79L Label NDC: 79458-000-02

Keep out of reach of children. If swallowed, get medical attention and contact poison control right away.

3.79L Label NDC: 79458-000-02

Wet hand and rub hands together until dry Children under 6 years of age should be supervised by an adult when using this product

3.79 L Label NDC: 79458-000-02

Store below 110^0 F (43^0 C)

3.79L Label NDC: 79458-000-02

Purified Water, Acrylates/vinyl crosspolymer

3.79L Label NDC: 79458-000-02

Antibacterial Hand Sanitizer

3.79 L Label NDC: 79458-000-02